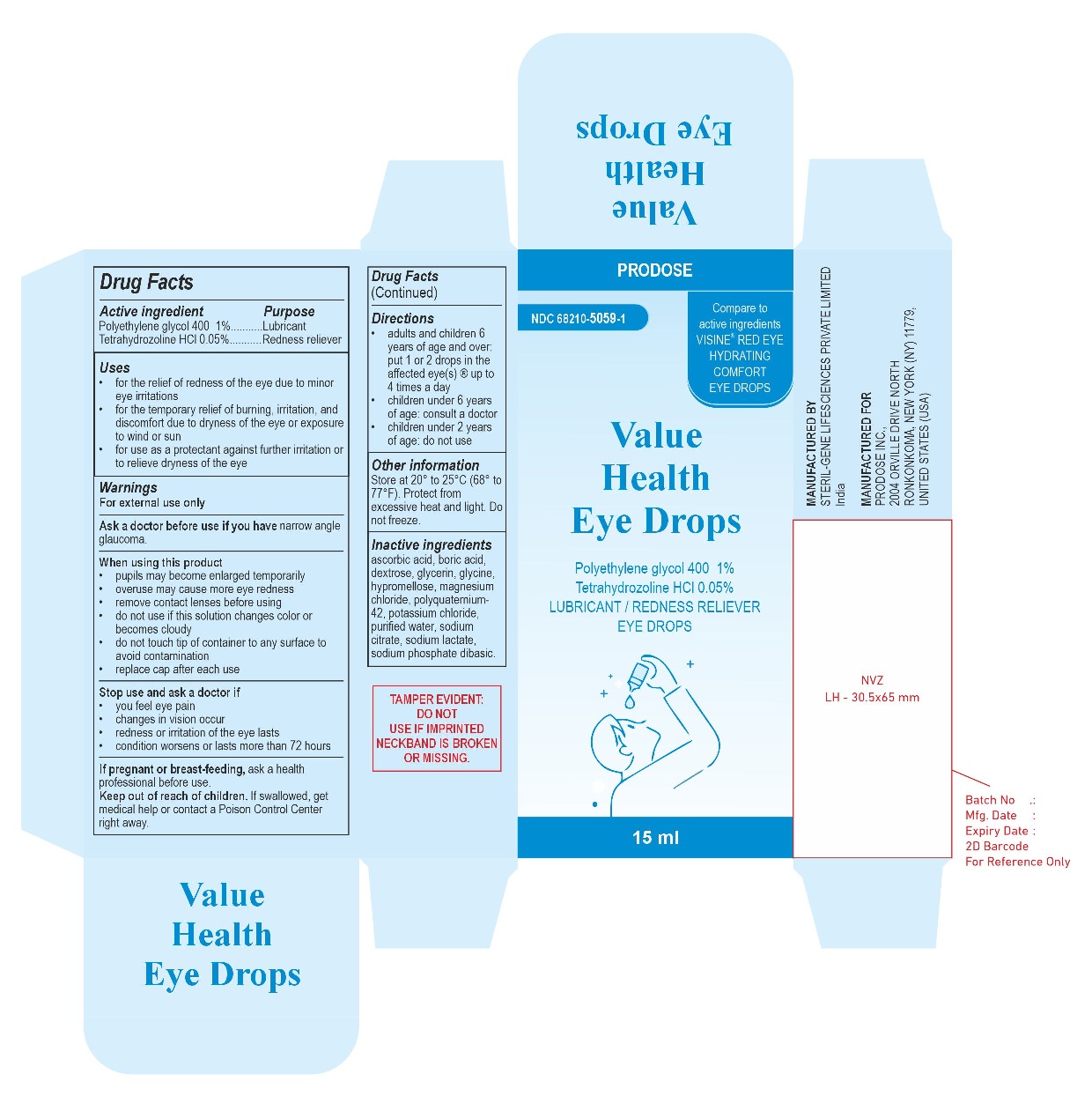 DRUG LABEL: Value Health by Prodose
NDC: 68210-5059 | Form: SOLUTION/ DROPS
Manufacturer: Prodose, Inc.
Category: otc | Type: HUMAN OTC DRUG LABEL
Date: 20251231

ACTIVE INGREDIENTS: TETRAHYDROZOLINE HYDROCHLORIDE 0.5 mg/1 mL; POLYETHYLENE GLYCOL 400 10 mg/1 mL
INACTIVE INGREDIENTS: BORIC ACID; ASCORBIC ACID; DEXTROSE, UNSPECIFIED FORM; GLYCERIN; GLYCINE; HYPROMELLOSE, UNSPECIFIED; MAGNESIUM CHLORIDE; POLIXETONIUM CHLORIDE; POTASSIUM CHLORIDE; WATER; SODIUM CITRATE, UNSPECIFIED FORM; SODIUM LACTATE; SODIUM PHOSPHATE, DIBASIC, ANHYDROUS

Value Health by Prodose Eye Drops

Drug Facts

ACTIVE INGREDIENT

Active ingredients | Purpose
Polyethylene glycol 400 1% | Lubricant
Tetrahydrozoline HCl 0.05% | Redness reliever

Uses

- for the relief of redness of the eye due to minor eye irritations
- for the temporary relief of burning, irritation, and discomfort due to dryness of the eye or exposure to wind or sun
- for use as a protectant against further irritation or to relieve dryness of the eye

Warnings

For external use only

Ask a doctor before use if you have narrow angle glaucoma.

When using this product

- pupils may become enlarged temporarily
- overuse may cause more eye redness
- remove contact lenses before using
- do not use if this solution changes color or becomes cloudy
- do not touch tip of container to any surface to avoid contamination
- replace cap after each use

Stop use and ask a doctor if

- you feel eye pain
- changes in vision occur
- redness or irritation of the eye lasts
- condition worsens or lasts more than 72 hours

PREGNANCY OR BREAST FEEDING

If pregnant or breast-feeding,ask a health professional before use.

Keep out of reach of children.If swallowed, get medical help or contact a Poison Control Center right away.

Directions

- adults and children 6 years of age and over: put 1 or 2 drops in the affected eye(s) up to 4 times a day
- children under 6 years of age: consult a doctor
- children under 2 years of age: do not use

Other information

Store at 20° to 25°C (68° to 77°F).Protect from excessive heat and light. Do not freeze.

Inactive ingredients

ascorbic acid, boric acid, dextrose, glycerin, glycine, hypromellose, magnesium chloride, polyquaternium-42, potassium chloride, purified water, sodium citrate, sodium lactate, sodium phosphate dibasic

PRINCIPAL DISPLAY PANEL - 15 mL Bottle Carton

PACK LABEL